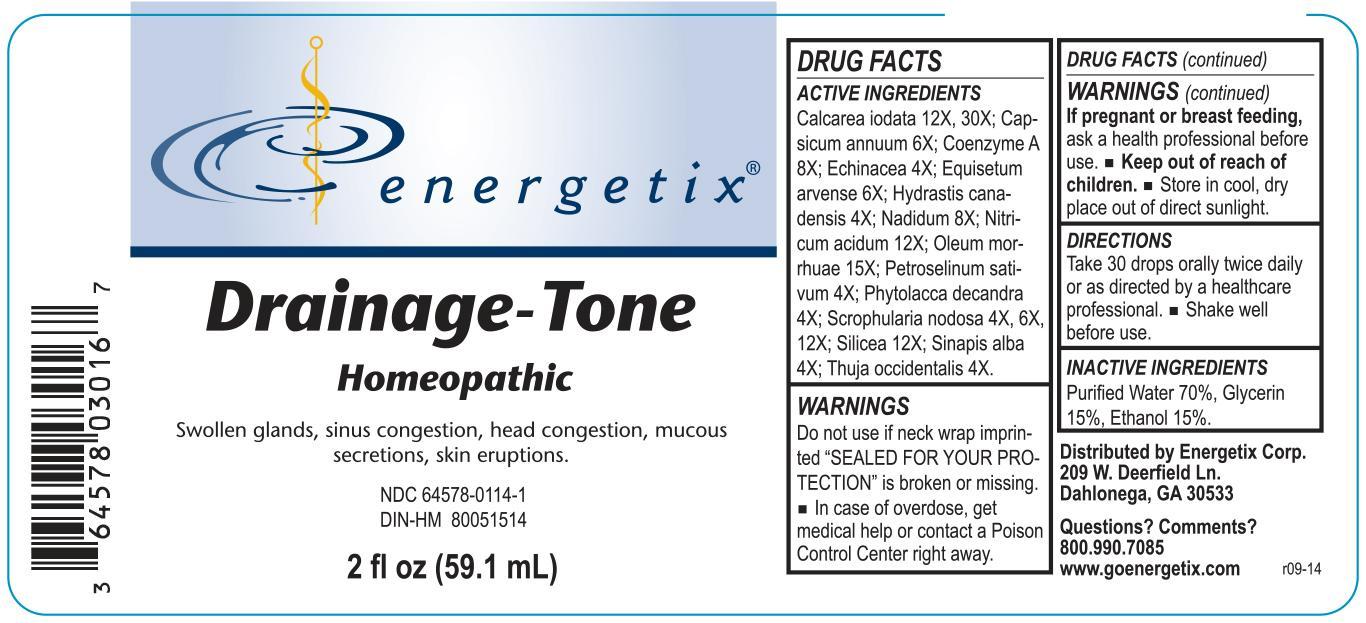 DRUG LABEL: Drainage-Tone
NDC: 64578-0114 | Form: LIQUID
Manufacturer: Energetix Corp
Category: homeopathic | Type: HUMAN OTC DRUG LABEL
Date: 20140924

ACTIVE INGREDIENTS: CALCIUM IODIDE 12 [hp_X]/59.1 mL; CAPSICUM 6 [hp_X]/59.1 mL; COENZYME A 8 [hp_X]/59.1 mL; ECHINACEA ANGUSTIFOLIA 4 [hp_X]/59.1 mL; EQUISETUM ARVENSE TOP 6 [hp_X]/59.1 mL; GOLDENSEAL 4 [hp_X]/59.1 mL; NADIDE 8 [hp_X]/59.1 mL; NITRIC ACID 12 [hp_X]/59.1 mL; COD LIVER OIL 15 [hp_X]/59.1 mL; PETROSELINUM CRISPUM 4 [hp_X]/59.1 mL; PHYTOLACCA AMERICANA ROOT 4 [hp_X]/59.1 mL; SCROPHULARIA NODOSA 4 [hp_X]/59.1 mL; SILICON DIOXIDE 12 [hp_X]/59.1 mL; WHITE MUSTARD SEED 4 [hp_X]/59.1 mL; THUJA OCCIDENTALIS LEAFY TWIG 4 [hp_X]/59.1 mL
INACTIVE INGREDIENTS: WATER 41.351 mL/59.1 mL; GLYCERIN 8.861 mL/59.1 mL; ALCOHOL 8.861 mL/59.1 mL

Drainage-Tone

ACTIVE INGREDIENT

Calcarea iodata 12X, 30X; Capsicum annuum 6X; Coenzyme A 8X; Echinacea 4X; Equisetum arvense 6X; Hydrastis canadensis 4X; Nadidum 8X; Nitricum acidum 12X; Oleum morrhuae 15X; Petroselinum sativum 4X; Phytolacca decandra 4X; Scrophularia nodosa 4X, 6X, 12X; Silicea 12X; Sinapis alba 4X; Thuja occidentalis 4X.

Do not use if neck wrap imprinted "SEALED FOR YOUR PROTECTION" is broken or missing.

OVERDOSAGE

In case of overdose, get medical help or contact a Poison Control Center right away.

PREGNANCY OR BREAST FEEDING

If pregnant or breast feeding, ask a health professional before use.

Keep out of reach of children.

STORAGE AND HANDLING

Store in cool, dry place out of direct sunlight.

Questions? Comments?
800.990.7085 www.goenergetix.com

PURPOSE

Swollen glands, sinus congestion, head congestion, mucous secretions, skin eruptions.

INACTIVE INGREDIENT

Purified Water 70%, Glycerin 15%, Ethanol 15%.

DOSAGE AND ADMINISTRATION

Take 30 drops orally twice daily or as directed by a healthcare professional. Shake well before use.

INDICATIONS AND USAGE

Swollen glands, sinus congestion, head congestion, mucous secretions, skin eruptions.